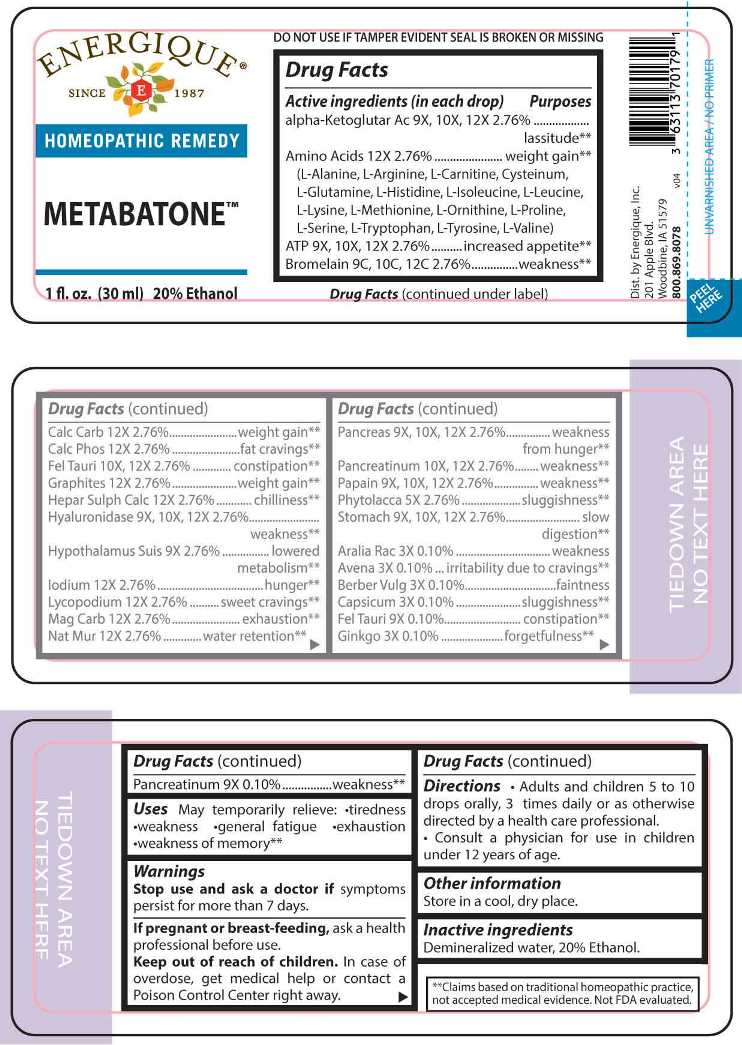 DRUG LABEL: Metabatone
NDC: 44911-0665 | Form: LIQUID
Manufacturer: Energique, Inc.
Category: homeopathic | Type: HUMAN OTC DRUG LABEL
Date: 20221228

ACTIVE INGREDIENTS: ARALIA RACEMOSA ROOT 3 [hp_X]/1 mL; AVENA SATIVA FLOWERING TOP 3 [hp_X]/1 mL; BERBERIS VULGARIS ROOT BARK 3 [hp_X]/1 mL; CAPSICUM 3 [hp_X]/1 mL; GINKGO 3 [hp_X]/1 mL; PHYTOLACCA AMERICANA ROOT 5 [hp_X]/1 mL; SUS SCROFA PITUITARY GLAND 9 [hp_X]/1 mL; ADENOSINE TRIPHOSPHATE DISODIUM 9 [hp_X]/1 mL; OXOGLURIC ACID 9 [hp_X]/1 mL; BOS TAURUS BILE 9 [hp_X]/1 mL; HYALURONIDASE (BOVINE) 9 [hp_X]/1 mL; SUS SCROFA PANCREAS 9 [hp_X]/1 mL; PANCRELIPASE 9 [hp_X]/1 mL; PAPAIN 9 [hp_X]/1 mL; SUS SCROFA STOMACH 9 [hp_X]/1 mL; ALANINE 12 [hp_X]/1 mL; ARGININE 12 [hp_X]/1 mL; LEVOCARNITINE 12 [hp_X]/1 mL; CYSTEINE 12 [hp_X]/1 mL; GLUTAMINE 12 [hp_X]/1 mL; HISTIDINE 12 [hp_X]/1 mL; ISOLEUCINE 12 [hp_X]/1 mL; LEUCINE 12 [hp_X]/1 mL; LYSINE 12 [hp_X]/1 mL; METHIONINE 12 [hp_X]/1 mL; ORNITHINE 12 [hp_X]/1 mL; PROLINE 12 [hp_X]/1 mL; SERINE 12 [hp_X]/1 mL; TRYPTOPHAN 12 [hp_X]/1 mL; TYROSINE 12 [hp_X]/1 mL; VALINE 12 [hp_X]/1 mL; OYSTER SHELL CALCIUM CARBONATE, CRUDE 12 [hp_X]/1 mL; TRIBASIC CALCIUM PHOSPHATE 12 [hp_X]/1 mL; GRAPHITE 12 [hp_X]/1 mL; CALCIUM SULFIDE 12 [hp_X]/1 mL; IODINE 12 [hp_X]/1 mL; LYCOPODIUM CLAVATUM SPORE 12 [hp_X]/1 mL; MAGNESIUM CARBONATE 12 [hp_X]/1 mL; SODIUM CHLORIDE 12 [hp_X]/1 mL; BROMELAINS 9 [hp_C]/1 mL
INACTIVE INGREDIENTS: WATER; ALCOHOL

DRUG FACTS:

ACTIVE INGREDIENTS:

(in each drop) Alpha-Ketoglutaricum Acidum 9X, 10X, 12X 2.76%, L-Alanine 12X 2.76%, L-Arginine 12X 2.76%, L-Carnitine 12X 2.76%, Cysteinum 12X 2.76%, L-Glutamine 12X 2.76%, L-Histidine 12X 2.76%, L-Isoleucine 12X 2.76%, L-Leucine 12X 2.76%, L-Lysine 12X 2.76%, L-Methionine 12X 2.76%, L-Ornithine 12X 2.76%, L-Proline 12X 2.76%, L-Serine 12X 2.76%, L-Tryptophan 12X 2.76% L-Tyrosine 12X 2.76%, L-Valine 12X 2.76%, Adenosinum Triphosphoricum Dinatrum 9X, 10X, 12X 2.76%, Bromelain 9C, 10C, 12C 2.76%, Calcarea Carbonica 12X 2.76%, Calcarea Phosphorica 12X2.76%, Fel Tauri 10X, 12X 2.76%, Graphites 12X 2.76%, Hepar Sulphuris Calcareum 12X 2.76%, Hyaluronidase 9X, 10X, 12X 2.76%, Hypothalamus Suis 9X 2.76%,Iodium 12X 2.76%, Lycopodium Clavatum 12X 2.76%, Magnesia Carbonica 12X 2.76%, Natrum Muriaticum 12X 2.76%, Pancreas Suis 9X, 10X, 12X 2.76%, Pancreatinum 10X, 12X 2.76%, Papain 9X, 10X, 12X 2.76%, Phytolacca Decandra 5X 2.76%, Stomach (Suis) 9X, 10X, 12X 2.76%, Aralia Racemosa 3X 0.10%, Avena Sativa 3X 0.10%, Berberis Vulgaris 3X 0.10%, Capsicum Annuum 3X 0.10%, Fel Tauri 9X 0.10%, Ginkgo Biloba 3X 0.10%, Pancreatinum 9X 0.10%.

PURPOSES:

Alpha-Ketoglutaricum Acidum – lassitude**, L-Alanine – weight gain**, L-Arginine - weight gain**, L-Carnitine - weight gain**, Cysteinum - weight gain**, L-Glutamine - weight gain**, L-Histidine - weight gain**, L-Isoleucine - weight gain**, L-Leucine - weight gain**, L-Lysine - weight gain**, L-Methionine - weight gain**, L-Ornithine - weight gain**, L-Proline - weight gain**, L-Serine - weight gain**, L-Tryptophan - weight gain**, L-Tyrosine - weight gain**, L-Valine - weight gain**, Adenosinum Triphosphoricum Dinatrum – increased appetite**, Bromelain – weakness**, Calcarea Carbonica – weight gain**, Calcarea Phosphorica – fat cravings**, Fel Tauri – constipation**, Graphites – weight gain **, Hepar Sulphuris Calcareum – chilliness **, Hyaluronidase – weakness**, Hypothalamus Suis – lowered metabolism **, Iodium – hunger**, Lycopodium Clavatum – sweet cravings**, Magnesia Carbonica – exhaustion**, Natrum Muriaticum – water retention**, Pancreas Suis – weakness for hunger**, Pancreatinum – weakness**, Papain – weakness**, Phytolacca Decandra – sluggishness**, Stomach (Suis) – slow digestion**, Aralia Racemosa – weakness**, Avena Sativa – irritability due to cravings**, Berberis Vulgaris – faintness**, Capsicum Annuum – sluggishness**, Ginkgo Biloba – forgetfulness**.

**Claims based on traditional homeopathic practice, not accepted medical evidence. Not FDA evaluated.

USES:

May temporarily relieve •tiredness •weakness •general fatigue •exhaustion •weakness of memory**

**Claims based on traditional homeopathic practice, not accepted medical evidence. Not FDA evaluated.

WARNINGS:

Stop use and ask a doctor if symptoms persist for more than 7 days.

If pregnant or breastfeeding, ask a health professional before use.

Keep out of reach of children. In case of overdose, get medical help or contact a Poison Control Center right away.
DO NOT USE IF TAMPER EVIDENT SEAL IS BRODEN OR MISSING
Store in a cool, dry place.

Keep out of reach of children. In case of overdose, get medical help or contact a Poison Control Center right away.

DIRECTIONS:

• Adults and children 5 to 10 drops orally, 3 times daily or as otherwise directed by a health care professional.

Consult a physician for use in children under 12 years of age.

INACTIVE INGREDIENTS:

Demineralized water, 20% Ethanol.

QUESTIONS:

Dist. by Energique, Inc.
201 Apple Blvd.
Woodbine, IA 51579

800.869.8078

PACKAGE LABEL DISPLAY:

ENERGIQUE

SINCE 1987

HOMEOPATHIC REMEDY

METABATONE

1 fl. oz. (30 ml)